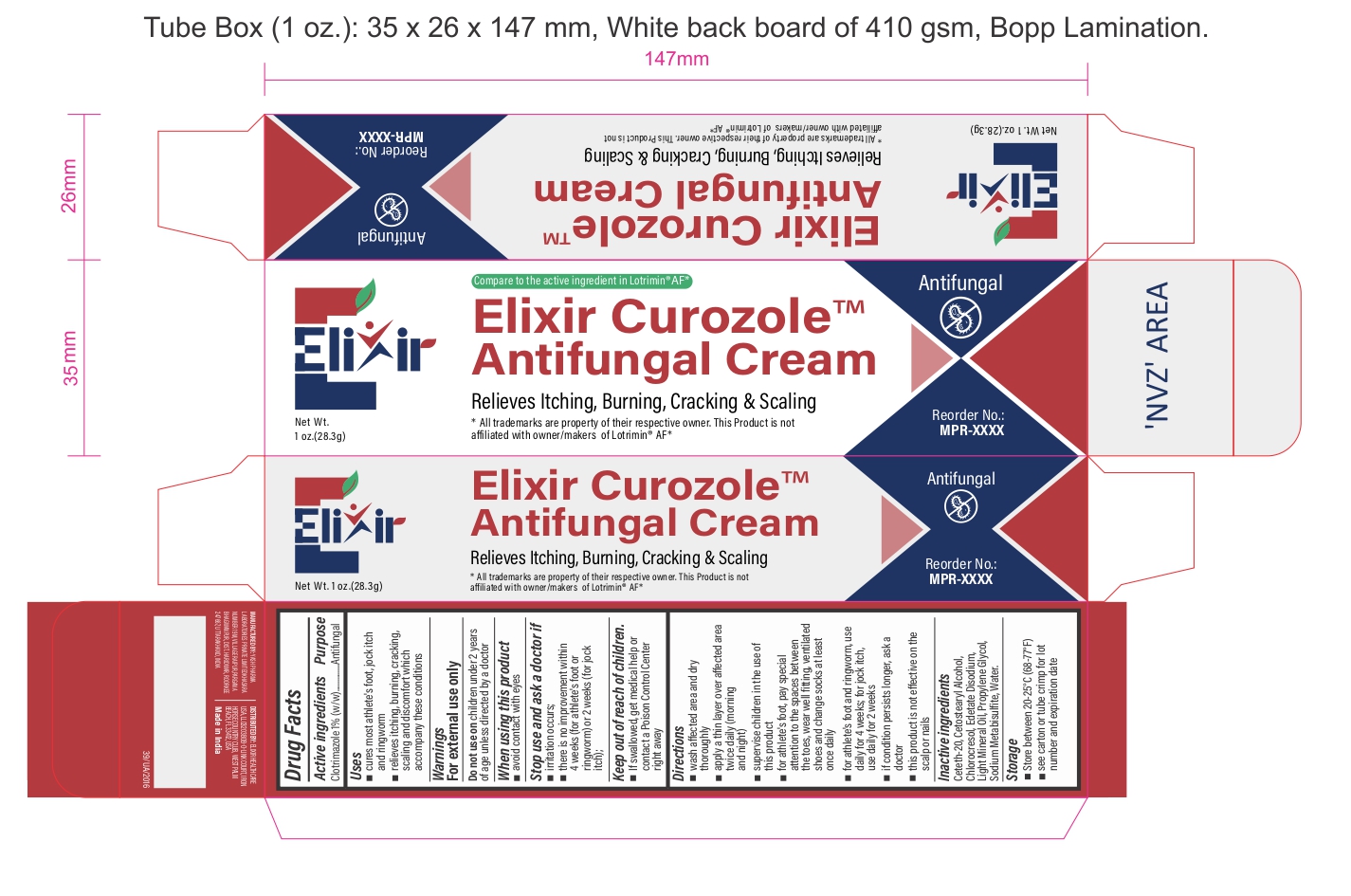 DRUG LABEL: ElixirCurozole
NDC: 84546-0003 | Form: CREAM
Manufacturer: ELIXIR HEALTHCARE USA, LLC.
Category: otc | Type: HUMAN OTC DRUG LABEL
Date: 20251226

ACTIVE INGREDIENTS: CLOTRIMAZOLE 1 g/100 g
INACTIVE INGREDIENTS: CETOSTEARYL ALCOHOL; CHLOROCRESOL; CETETH-20; SODIUM METABISULFITE; DISODIUM EDTA-COPPER; MINERAL OIL; PROPYLENE GLYCOL; GLYCERYL MONOSTEARATE

ElixirCurozole Clotrimazole Topical Solution USP,1%

Active Ingredients

Clotrimazole 1% (w/w)

Purposes

Antifungal

Uses

- cures most athlete's foot, jock itch and ringworm
- relieves itching, burning, cracking, scaling and discomfort which accompany these conditions

Warnings

For external use only

When using this product avoid contact with eyes

Stop use and ask a doctor if

• irritation occurs;
• there is no improvement within 4 weeks (for athlete's foot or ringworm) or 2 weeks (for jock itch);

KEEP OUT OF REACH OF CHILDREN

If swallowed, get medical help or contact a Poison Control Center right away

Directions

- wash affected area and dry thoroughly
- apply a thin layer over affected area twice daily (morning and night)
- supervise children in the use of this product
- for athlete's foot, pay special attention to the spaces between the toes, wear well fitting, ventilated shoes and change socks at least once daily
- for athlete's foot and ringworm, use daily for 4 weeks; for jock itch, use daily for 2 weeks
- if condition persists longer, ask a doctor
- this product is not effective on the scalp or nails

Other information

store at 20-25°C (68-77°F)

Inactive ingredients

Ceteth-20, Cetostearyl Alcohol, Chlorocresol, Edetate Disodium, Light Mineral Oil, Propylene Glycol, Sodium Metabisulfite, Water.

PRINCIPAL DISPLAY PANEL

Elixir

Net Wt. 1 oz. (28.3g)

Compare to the active ingredient in lotrimin AF*

ELIXIR CUROZOLETM

Antifungal

Relieves Itching, Burning, Cracking & Scaling

*All tradmarks are property of their respective owner. This product is not affiliated with onwer/makers of Lotrimin AF*

Reorder No:

MPR-XXXX